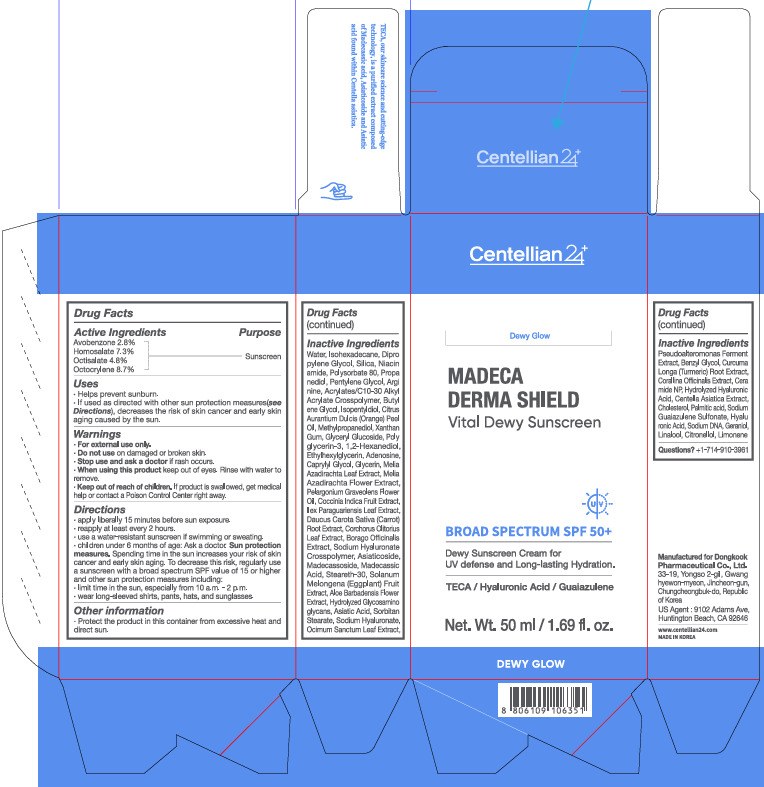 DRUG LABEL: Centellian24 Madeca Derma Shield Vital Dewy Sunscreen
NDC: 70541-210 | Form: CREAM
Manufacturer: 70541
Category: otc | Type: HUMAN OTC DRUG LABEL
Date: 20251201

ACTIVE INGREDIENTS: AVOBENZONE 2.8 g/100 mL; HOMOSALATE 7.3 g/100 mL; OCTISALATE 4.8 g/100 mL; OCTOCRYLENE 8.7 g/100 mL
INACTIVE INGREDIENTS: WATER

Dosage and administrations

Directions
· apply liberally 15 minutes before sun exposure.
· reapply at least every 2 hours.
· use a water-resistant sunscreen if swimming or sweating.
· children under 6 months of age: Ask a doctor. Sun protection measures. Spending time in the sun increases your risk of skin cancer and early skin aging. To decrease this risk, regularly use a sunscreen with a broad spectrum SPF value of 15 or higher and other sun protection measures including:
· limit time in the sun, especially from 10 a.m. – 2 p.m.
· wear long-sleeved shirts, pants, hats, and sunglasses.

Warnings

· For external use only.
· Do not use on damaged or broken skin.
· Stop use and ask a doctor if rash occurs.
· When using this product keep out of eyes. Rinse with water to remove.
· Keep out of reach of children. If product is swallowed, get medical help or contact a Poison Control Center right away.

INACTIVE INGREDIENT

Inactive Ingredients
Water, Isohexadecane, Dipropylene Glycol, Silica, Niacinamide, Polysorbate 80, Propanediol, Pentylene Glycol, Arginine, Acrylates/C10-30 Alkyl Acrylate Crosspolymer, Butylene Glycol, Isopentyldiol, Citrus Aurantium Dulcis (Orange) Peel Oil, Methylpropanediol, Xanthan Gum, Glyceryl Glucoside, Polyglycerin-3, 1,2-Hexanediol, Ethylhexylglycerin, Adenosine, Caprylyl Glycol, Glycerin, Melia Azadirachta Leaf Extract, Melia Azadirachta Flower Extract, Pelargonium Graveolens Flower Oil, Coccinia Indica Fruit Extract, Ilex Paraguariensis Leaf Extract, Daucus Carota Sativa (Carrot) Root Extract, Corchorus Olitorius Leaf Extract, Borago Officinalis Extract, Sodium Hyaluronate Crosspolymer, Asiaticoside, Madecassoside, Madecassic Acid, Steareth-30, Solanum Melongena (Eggplant) Fruit Extract, Aloe Barbadensis Flower Extract, Hydrolyzed Glycosaminoglycans, Asiatic Acid, Sorbitan Stearate, Sodium Hyaluronate, Ocimum Sanctum Leaf Extract,
Pseudoalteromonas Ferment Extract, Benzyl Glycol, Curcuma Longa (Turmeric) Root Extract, Corallina Officinalis Extract, Ceramide NP, Hydrolyzed Hyaluronic Acid, Centella Asiatica Extract, Cholesterol, Palmitic acid, Sodium Guaiazulene Sulfonate, Hyaluronic Acid, Sodium DNA, Geraniol, Linalool, Citronellol, Limonene

Uses

· Helps prevent sunburn.
· If used as directed with other sun protection measures (see Directions), decreases the risk of skin cancer and early skin aging caused by the sun.

Keep out of reach of children. If product is swallowed, get medical help or contact a Poison Control Center right away.

Purpose

Sunscreen